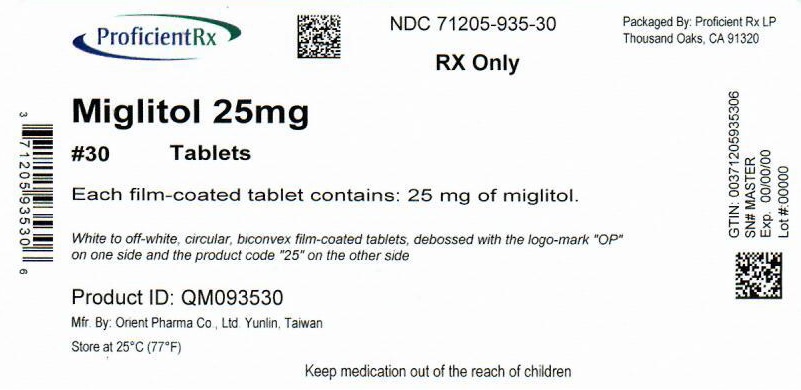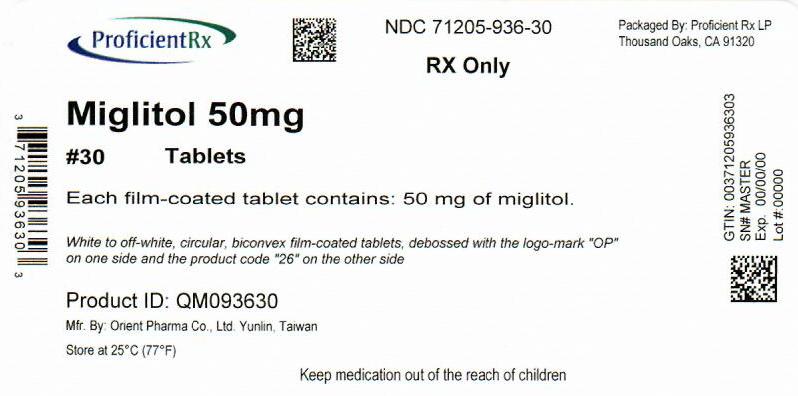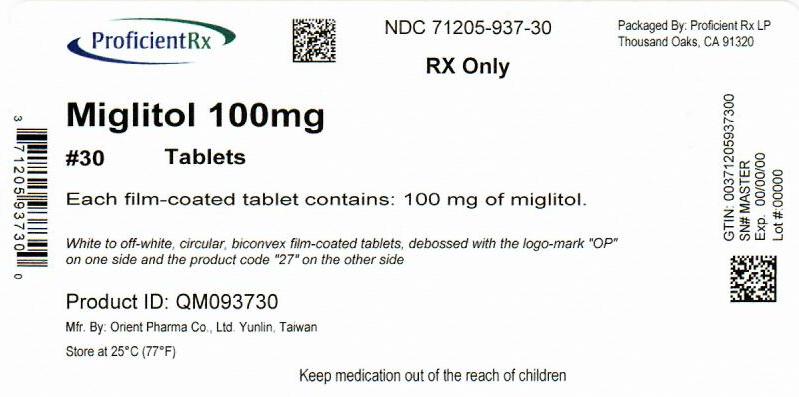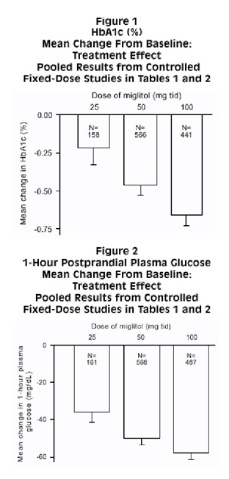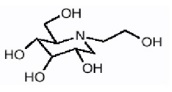 DRUG LABEL: Miglitol
NDC: 71205-935 | Form: TABLET, COATED
Manufacturer: Proficient Rx LP
Category: prescription | Type: HUMAN PRESCRIPTION DRUG LABEL
Date: 20220401

ACTIVE INGREDIENTS: MIGLITOL 25 mg/1 1
INACTIVE INGREDIENTS: MAGNESIUM STEARATE; MICROCRYSTALLINE CELLULOSE; STARCH, CORN; HYPROMELLOSE, UNSPECIFIED; POLYETHYLENE GLYCOL 400; TITANIUM DIOXIDE; POLYSORBATE 80

Miglitol Tablets

For Oral Use

DESCRIPTION

Miglitol Tablets, an oral alpha-glucosidase inhibitor for use in the management of non-insulin-dependent diabetes mellitus (NIDDM). Miglitol is a desoxynojirimycin derivative, and is chemically known as 3,4,5-piperidinetriol, 1-(2-hydroxyethyl) -2-(hydroxymethyl)-, [2R-(2a,3ß,4a, 5ß)]-. It is a white to pale-yellow powder with a molecular weight of 207.2. Miglitol is soluble in water and has a pK a of 5.9. Its empirical formula is C 8 H 17 NO 5 and its chemical structure is as follows:

Miglitol tablets are available as 25 mg, 50 mg, and 100 mg tablets for oral use. The inactive ingredients are corn starch, microcrystalline cellulose, magnesium stearate, hypromelloses, polyethylene glycols, titanium dioxide, and polysorbate 80.

CLINICAL PHARMACOLOGY

Miglitol is a desoxynojirimycin derivative that delays the digestion of ingested carbohydrates, thereby resulting in a smaller rise in blood glucose concentration following meals. As a consequence of plasma glucose reduction, miglitol tablets reduce levels of glycosylated hemoglobin in patients with Type II (non-insulin-dependent) diabetes mellitus. Systemic nonenzymatic protein glycosylation, as reflected by levels of glycosylated hemoglobin, is a function of average blood glucose concentration over time.

Mechanism of Action

In contrast to sulfonylureas, miglitol tablets do not enhance insulin secretion. The antihyperglycemic action of miglitol results from a reversible inhibition of membrane-bound intestinal α-glucoside hydrolase enzymes. Membrane-bound intestinal α-glucosidases hydrolyze oligosaccharides and disaccharides to glucose and other monosaccharides in the brush border of the small intestine. In diabetic patients, this enzyme inhibition results in delayed glucose absorption and lowering of postprandial hyperglycemia.

Because its mechanism of action is different, the effect of miglitol tablets to enhance glycemic control is additive to that of sulfonylureas when used in combination. In addition, miglitol tablets diminish the insulinotropic and weight-increasing effects of sulfonylureas.

Miglitol has minor inhibitory activity against lactase and consequently, at the recommended doses, would not be expected to induce lactose intolerance.

Pharmacokinetics

Absorption

Absorption of miglitol is saturable at high doses: a dose of 25 mg is completely absorbed, whereas a dose of 100 mg is 50% to 70% absorbed. For all doses, peak concentrations are reached in 2 to 3 hours. There is no evidence that systemic absorption of miglitol contributes to its therapeutic effect.

Distribution

The protein binding of miglitol is negligible (<4.0%). Miglitol has a volume of distribution of 0.18 L/kg, consistent with distribution primarily into the extracellular fluid.

Metabolism

Miglitol is not metabolized in humans or in any animal species studied. No metabolites have been detected in plasma, urine, or feces, indicating a lack of either systemic or pre-systemic metabolism.

Excretion

Miglitol is eliminated by renal excretion as unchanged drug. Following a 25 mg dose, over 95% of the dose is recovered in the urine within 24 hours. At higher doses, the cumulative recovery of drug from urine is somewhat lower due to the incomplete bioavailability. The elimination half-life of miglitol from plasma is approximately 2 hours.

Special Populations

Renal Impairment

Because miglitol is excreted primarily by the kidneys, accumulation of miglitol is expected in patients with renal impairment. Patients with creatinine clearance <25 mL/min taking 25 mg 3 times daily, exhibited a greater than two-fold increase in miglitol plasma levels as compared to subjects with creatinine clearance >60 mL/min. Dosage adjustment to correct the increased plasma concentrations is not feasible because miglitol acts locally. Little information is available on the safety of miglitol in patients with creatinine clearance <25 mL/min. Therefore, treatment of these patients with miglitol is not recommended.

Hepatic impairment

Miglitol pharmacokinetics were not altered in cirrhotic patients relative to healthy control subjects. Since miglitol is not metabolized, no influence of hepatic function on the kinetics of miglitol is expected.

Gender

No significant difference in the pharmacokinetics of miglitol was observed between elderly men and women when body weight was considered.

Race

Several pharmacokinetic studies were conducted in Japanese volunteers, with results similar to those observed in Caucasians. A study comparing the pharmacodynamic response to a single 50 mg dose in Black and Caucasian healthy volunteers indicated similar glucose and insulin responses in both populations.

CLINICAL STUDIES

Clinical Experience in Non-Insulin-Dependent Diabetes Mellitus (NIDDM) Patients on Dietary Treatment Only

Miglitol tablets were evaluated in two U.S. and three non-U.S. controlled, fixed-dose, monotherapy studies, in which 735 patients treated with miglitol tablets were evaluated for efficacy analyses (see Error! Hyperlink reference not valid.).

In Study 1, a 1-year study in which miglitol tablets were evaluated as monotherapy and also as combination therapy, there was a statistically significantly smaller increase in mean glycosylated hemoglobin (HbA1c) over time in the miglitol 50 mg 3 times daily monotherapy arm compared to placebo. Significant reductions in mean fasting and postprandial plasma glucose levels and in mean postprandial insulin levels were observed in patients treated with miglitol tablets compared with the placebo group.

In Study 2, a 14-week study, there was a significant decrease in HbA1c in patients receiving miglitol tablets 50 mg 3 times daily or 100 mg 3 times daily compared to placebo. In addition, there were significant reductions in postprandial plasma glucose and postprandial serum insulin levels compared to placebo.

Study 3 was a 6-month dose-ranging trial evaluating miglitol tablets at doses from 25 mg 3 times daily, to 200 mg 3 times daily. Miglitol tablets produced a greater reduction in HbA1c than placebo at all doses, although the effect was statistically significant at the 100 mg 3 times daily and 200 mg 3 times daily. In addition, all doses of miglitol tablets produced significant reductions in postprandial plasma glucose and postprandial insulin levels compared to placebo.

Studies 4 and 5 were 6-month studies evaluating miglitol tablets at 50 and 100 mg 3 times daily, and 100 mg 3 times daily, respectively. As compared to placebo, miglitol tablets produced reductions in HbA1c, as well as a significant reduction in postprandial plasma glucose in both studies at the doses employed.

Table 1 Results of Monotherapy Study with Miglitol Tablets

 |  | HbA1c (%) |  | 1-hour Postprandial Glucose (mg/dL)
Study | Treatment | Mean Change from Baseline [Mean baseline ranged from 7.54 to 8.72% in these studies.] | Treatment Effect [The result of subtracting the placebo group average.] | Mean Change from Baseline | Treatment Effect ^2
1 | Placebo | +0.71 | --- | +24 | ---
(U.S.) | Miglitol tablets 50 mg 3 times daily | +0.13 | -0.58 [p≤ 0.05] | -39 | -63 ^3
2 | Placebo | +0.47 | --- | +15 | ---
(U.S.) | Miglitol tablets 50 mg 3 times daily | -0.22 | -0.69 ^3 | -52 | -67 ^3
 | Miglitol tablets 100 mg 3 times daily | -0.28 | -0.75 ^3 | -59 | -74 ^3
3 | Placebo | +0.18 | --- | +2 | ---
(non-U.S.) | Miglitol tablets 25 mg 3 times daily | -0.08 | -0.26 | -33 | -35 ^3
(non-U.S.) | Miglitol tablets 50 mg 3 times daily | -0.22 | -0.40 | -45 | -47 ^3
(non-U.S.) | Miglitol tablets 100 mg 3 times daily | -0.63 | -0.81 ^3 | -62 | -64 ^3
(non-U.S.) | Miglitol tablets 200 mg 3 times daily [Although results for the 200 mg 3 times daily are presented for completeness, the maximum recommended dosage of Miglitol tablets is 100 mg 3 times daily.] | -0.84 | -1.02 ^3 | -85 | -87 ^3
4 | Placebo | +0.01 | --- | +8 | ---
(non-U.S.) | Miglitol tablets 50 mg 3 times daily | -0.35 | -0.36 ^3 | -20 | -28 ^3
(non-U.S.) | Miglitol tablets 100 mg 3 times daily | -0.57 | -0.58 ^3 | -25 | -33 ^3
5 | Placebo | +0.32 | --- | +17 | ---
(non-U.S.) | Miglitol tablets 100 mg 3 times daily | -0.43 | -0.75 ^3 | -38 | -55 ^3

Clinical Experience in NIDDM Patients Receiving Sulfonylureas

Miglitol tablets were studied as adjunctive therapy to a background of maximal or near-maximal sulfonylurea (SFU) treatment in three large, double-blind, randomized studies (two U.S. and one non-U.S.) in which 471 patients treated with miglitol tablets were evaluated for efficacy (see Error! Hyperlink reference not valid.).

Study 6 included patients under treatment with maximal doses of SFU at entry. At the end of this 14-week study, the mean treatment effects on glycosylated hemoglobin (HbA1c) were -0.82% and -0.74% for patients receiving miglitol tablets 50 mg 3 times daily plus SFU, and miglitol tablets 100 mg 3 times daily plus SFU, respectively.

Study 7 was a 1-year study in which miglitol tablets at 25, 50 or 100 mg 3 times daily was added to a maximal dose of glyburide (10 mg twice daily). At the end of this study, the mean treatment effects on HbA1c of miglitol tablets when added to maximum glyburide therapy were -0.30%, -0.62%, and -0.73% with the 25, 50 and 100 mg 3 times daily dosages of miglitol tablets, respectively.

In Study 8, the addition of miglitol tablets 100 mg 3 times daily to a background of treatment with glyburide produced an additional mean treatment effect on HbA1c of -0.66%.

Table 2 Results of Combination Therapy with Miglitol Tablets Plus Sulfonylurea (SFU)
 |  | HbA1c (%) |  | 1-hour Postprandial Glucose (mg/dL)
Study | Treatment | Mean Change from Baseline [Mean baseline ranged from 8.56 to 9.16% in these studies.] | Treatment Effect [The result of subtracting the placebo group average.] | Mean Change from Baseline | Treatment Effect ^2
6 | Placebo + SFU | +0.33 | --- | -1 | ---
(U.S.) | Miglitol tablets 50 mg 3 times daily + SFU | -0.49 | -0.82 [p≤ 0.05] | -69 | -68 ^3
 | Miglitol tablets 100 mg 3 times daily + SFU | -0.41 | -0.74 ^3 | -73 | -72 ^3
7 | Placebo + SFU | +1.01 | --- | 48 | ---
(U.S.) | Miglitol tablets 25 mg 3 times daily + SFU | +0.71 | -0.30 | -2 | -50 ^3
 | Miglitol tablets 50 mg 3 times daily + SFU | +0.39 | -0.62 ^3 | -13 | -61 ^3
 | Miglitol tablets 100 mg 3 times daily + SFU | +0.28 | -0.73 ^3 | -33 | -81 ^3
8 | Placebo + SFU | +0.16 | --- | +10 | ---
(non-U.S.) | Miglitol tablets 100 mg 3 times daily + SFU | -0.50 | -0.66 ^3 | -36 | -46 ^3

Dose-Response

Results from controlled, fixed-dose studies of miglitol tablets as monotherapy or as combination treatment with a sulfonylurea were combined to derive a pooled estimate of the difference from placebo in the mean change from baseline in glycosylated hemoglobin (HbA1c) and postprandial plasma glucose as shown in Figures 1 and 2:

Because of its mechanism of action, the primary pharmacologic effect of miglitol is manifested as a reduction in postprandial plasma glucose, as shown previously in all of the major clinical trials. Miglitol tablets were statistically significantly different from placebo at all doses in each of the individual studies with respect to effect on mean one-hour postprandial plasma glucose, and there is a dose response from 25 to 100 mg 3 times daily for this efficacy parameter.

INDICATIONS AND USAGE

Miglitol tablets are indicated as an adjunct to diet and exercise to improve glycemic control in adults with type 2 diabetes mellitus.

CONTRAINDICATIONS

Miglitol tablets are contraindicated in patients with:

- Diabetic ketoacidosis
- Inflammatory bowel disease, colonic ulceration, or partial intestinal obstruction, and in patients predisposed to intestinal obstruction
- Chronic intestinal diseases associated with marked disorders of digestion or absorption, or with conditions that may deteriorate as a result of increased gas formation in the intestine
- Hypersensitivity to the drug or any of its components

PRECAUTIONS

Macrovascular Outcomes

There have been no clinical studies establishing conclusive evidence of macrovascular risk reduction with miglitol tablets or any other anti-diabetic drug.

General

Hypoglycemia

Because of its mechanism of action, miglitol tablets, when administered alone should not cause hypoglycemia in the fasted or postprandial state. Sulfonylureas and insulin can cause hypoglycemia. Because miglitol tablets given in combination with a sulfonylurea or insulin will cause a further lowering of blood glucose, it may increase the hypoglycemic potential of the sulfonylurea or insulin. Consider reducing the dose of sulfonylureas or insulin when miglitol tablets are used in combination with these medications.

Oral glucose (dextrose), whose absorption is not delayed by miglitol tablets, should be used instead of sucrose (cane sugar) in the treatment of mild-to-moderate hypoglycemia. Sucrose, whose hydrolysis to glucose and fructose is inhibited by miglitol tablets, is unsuitable for the rapid correction of hypoglycemia. Severe hypoglycemia may require the use of either intravenous glucose infusion or glucagon injection.

Loss of Control of Blood Glucose

When diabetic patients are exposed to stress such as fever, trauma, infection, or surgery, a temporary loss of control of blood glucose may occur. At such times, temporary insulin therapy may be necessary.

Renal Impairment

Plasma concentrations of miglitol tablets in renally impaired volunteers were proportionally increased relative to the degree of renal dysfunction. Long-term clinical trials in diabetic patients with significant renal dysfunction (serum creatinine >2.0 mg/dL) have not been conducted. Therefore, treatment of these patients with miglitol tablets is not recommended.

Information for Patients

The following information should be provided to patients:

- Miglitol tablets should be taken orally three times a day at the start of each main meal. It is important to continue to adhere to dietary instructions, a regular exercise program, and regular testing of urine and/or blood glucose.
- Miglitol tablets themselves do not cause hypoglycemia when administered to patients in the fasted state. Sulfonylurea drugs and insulin, however, can lower blood sugar levels and cause symptoms or life-threatening hypoglycemia. Because miglitol tablets given in combination with a sulfonylurea or insulin will cause a further lowering of blood sugar, it may increase the hypoglycemic potential of these agents. The risk of hypoglycemia, its symptoms and treatment, and conditions that predispose to its development should be well understood by patients and responsible family members. Because miglitol tablets prevent the breakdown of table sugar, a source of glucose (dextrose, D-glucose) should be readily available to treat symptoms of low blood sugar when taking miglitol tablets in combination with a sulfonylurea or insulin.
- If side effects occur with miglitol tablets, they usually develop during the first few weeks of therapy. They are most commonly mild-to-moderate dose-related gastrointestinal effects, such as flatulence, soft stools, diarrhea, or abdominal discomfort, and generally diminish in frequency and intensity with time. Discontinuation of drug usually results in rapid resolution of these gastrointestinal symptoms.

Physician Counseling Information for Patients

In initiating treatment for type 2 diabetes, diet should be emphasized as the primary form of treatment. Caloric restriction and weight loss are essential in the obese diabetic patient. Proper dietary management alone may be effective in controlling the blood glucose and symptoms of hyperglycemia. The importance of regular physical activity should also be stressed, and cardiovascular risk factors should be identified and corrective measures taken where possible. Use of miglitol tablets or other antidiabetic medications must be viewed by both the physician and patient as a treatment in addition to diet and not as a substitution or as a convenient mechanism for avoiding dietary restraint. Furthermore, loss of blood glucose control on diet alone may be transient, thus requiring only short-term administration of miglitol tablets or other antidiabetic medications. Maintenance or discontinuation of miglitol tablets or other antidiabetic medications should be based on clinical judgment using regular clinical and laboratory evaluations.

Laboratory Tests

Therapeutic response to miglitol tablets may be monitored by periodic blood glucose tests. Measurement of glycosylated hemoglobin levels is recommended for the monitoring of long-term glycemic control.

Drug Interactions

Several studies investigated the possible interaction between miglitol and glyburide. In six healthy volunteers given a single dose of 5 mg glyburide on a background of 6 days treatment with miglitol (50 mg 3 times daily for 4 days followed by 100 mg 3 times daily for 2 days) or placebo, the mean C max and AUC values for glyburide were 17% and 25% lower, respectively, when glyburide was given with miglitol. In a study in diabetic patients in which the effects of adding miglitol 100 mg 3 times daily for 7 days or placebo to a background regimen of 3.5 mg glyburide daily were investigated, the mean AUC value for glyburide was 18% lower in the group treated with miglitol, although this difference was not statistically significant. Information on a potential interaction with glyburide was obtained from one of the large U.S. clinical trials (Study 7) in which patients were dosed with either miglitol or placebo on a background of glyburide 10 mg twice daily. At the 6-month and 1-year clinic visits, patients taking concomitant miglitol 100 mg 3 times daily exhibited mean C max values for glyburide that were 16% and 8% lower, respectively, compared to patients taking glyburide alone. However, these differences were not statistically significant. Thus, although there was a trend toward lower AUC and C max values for glyburide when co-administered with miglitol tablets, no definitive statement regarding a potential interaction can be made based on the foregoing three studies.

The effect of miglitol (100 mg 3 times daily for 7 days) on the pharmacokinetics of a single 1000 mg dose of metformin was investigated in healthy volunteers. Mean AUC and C max values for metformin were 12% to 13% lower when the volunteers were given miglitol as compared with placebo, but this difference was not statistically significant.

In a study with healthy volunteers, co-administration of either 50 mg or 100 mg miglitol 3 times daily together with digoxin reduced the average plasma concentrations of digoxin by 19% and 28%, respectively. However, in diabetic patients under treatment with digoxin, plasma digoxin concentrations were not altered by co-administration of miglitol 100 mg 3 times daily for 14 days.

Other healthy volunteer studies have demonstrated that miglitol may significantly reduce the bioavailability of ranitidine and propranolol by 60% and 40%, respectively. No effect of miglitol was observed on the pharmacokinetics or pharmacodynamics of either warfarin or nifedipine.

Intestinal adsorbents (e.g., charcoal) and digestive enzyme preparations containing carbohydrate-splitting enzymes (e.g., amylase, pancreatin) may reduce the effect of miglitol tablets and should not be taken concomitantly.

In 12 healthy males, concomitantly administered antacid did not influence the pharmacokinetics of miglitol.

Carcinogenesis, Mutagenesis, and Impairment of Fertility

Miglitol was administered to mice by the dietary route at doses as high as approximately 500 mg/kg body weight (corresponding to greater than 5 times the exposure in humans based on AUC) for 21 months. In a two-year rat study, miglitol was administered in the diet at exposures comparable to the maximum human exposures based on AUC. There was no evidence of carcinogenicity resulting from dietary treatment with miglitol.

In vitro, miglitol was found to be nonmutagenic in the bacterial mutagenesis (Ames) assay and the eukaryotic forward mutation assay (CHO/HGPRT). Miglitol did not have any clastogenic effects in vivo in the mouse micronucleus test. There were no heritable mutations detected in dominant lethal assay.

A combined male and female fertility study conducted in Wistar rats treated orally with miglitol at dose levels of 300 mg/kg body weight (approximately 8 times the maximum human exposure based on body surface area) produced no untoward effect on reproductive performance or capability to reproduce. Survival, growth, development, and fertility of the offspring were not compromised.

Pregnancy

Teratogenic Effects

Pregnancy Category B

The safety of miglitol tablets in pregnant women has not been established. Developmental toxicology studies have been performed in rats at doses of 50, 150 and 450 mg/kg, corresponding to levels of approximately 1.5, 4, and 12 times the maximum recommended human exposure based on body surface area. In rabbits, doses of 10, 45, and 200 mg/kg corresponding to levels of approximately 0.5, 3, and 10 times the human exposure were examined. These studies revealed no evidence of fetal malformations attributable to miglitol. Doses of miglitol up to 4 and 3 times the human dose (based on body surface area), for rats and rabbits respectively, did not reveal evidence of impaired fertility or harm to the fetus. The highest doses tested in these studies, 450 mg/kg in the rat and 200 mg/kg in the rabbit promoted maternal and/or fetal toxicity. Fetotoxicity was indicated by a slight but significant reduction in fetal weight in the rat study and slight reduction in fetal weight, delayed ossification of the fetal skeleton and increase in the percentage of non-viable fetuses in the rabbit study. In the peri-postnatal study in rats, the NOAEL (No Observed Adverse Effect Level) was 100 mg/kg (corresponding to approximately four times the exposure to humans, based on body surface area). An increase in stillborn progeny was noted at the high dose (300 mg/kg) in the rat peri-postnatal study, but not at the high dose (450 mg/kg) in the delivery segment of the rat developmental toxicity study. Otherwise, there was no adverse effect on survival, growth, development, behavior, or fertility in either the rat developmental toxicity or peri-postnatal studies. There are however, no adequate and well-controlled studies in pregnant women. Because animal reproduction studies are not always predictive of human response, miglitol should be used during pregnancy only if clearly needed.

Nursing Mothers

Miglitol has been shown to be excreted in human milk to a very small degree. Total excretion into milk accounted for 0.02% of a 100 mg maternal dose. The estimated exposure to a nursing infant is approximately 0.4% of the maternal dose. Although the levels of miglitol reached in human milk are exceedingly low, it is recommended that miglitol tablets not be administered to a nursing woman.

Pediatric Use

Safety and effectiveness of miglitol tablets in pediatric patients have not been established.

Geriatric Use

Of the total number of subjects in clinical studies of miglitol tablets in the United States, patients valid for safety analyses included 24% over 65, and 3% over 75. No overall differences in safety and effectiveness were observed between these subjects and younger subjects. The pharmacokinetics of miglitol were studied in elderly and young males (n=8 per group). At the dosage of 100 mg 3 times daily for 3 days, no differences between the two groups were found.

ADVERSE REACTIONS

Gastrointestinal

Gastrointestinal symptoms are the most common reactions to miglitol tablets. In U.S. placebo-controlled trials, the incidences of abdominal pain, diarrhea, and flatulence were 11.7%, 28.7%, and 41.5% respectively in 962 patients treated with miglitol tablets, 25 mg to 100 mg 3 times daily, whereas the corresponding incidences were 4.7%, 10.0%, and 12.0% in 603 placebo-treated patients. The incidence of diarrhea and abdominal pain tended to diminish with continued treatment.

Dermatologic

Skin rash was reported in 4.3% of patients treated with miglitol tablets compared to 2.4% of placebo-treated patients. Rashes were generally transient and most were assessed as unrelated to miglitol tablets by physician investigators.

Abnormal Laboratory Findings

Low serum iron occurred more often in patients treated with miglitol tablets (9.2%) than in placebo-treated patients (4.2%) but did not persist in the majority of cases and was not associated with reductions in hemoglobin or changes in other hematologic indices.

Postmarketing Experience

The following adverse reactions have been reported during post-approval use of miglitol tablets. Because these reactions are reported voluntarily from a population of uncertain size, it is generally not possible to reliably estimate their frequency or establish a causal relationship to drug exposure.

Gastrointestinal Disorders: ileus (including paralytic ileus), subileus, gastrointestinal pain, nausea, abdominal distention.

- Pneumatosis Cystoides Intestinalis

There have been rare postmarketing reports of pneumatosis cystoides intestinalis associated with the use of alpha-glucosidase inhibitors, including miglitol tablets. Pneumatosis cystoides intestinalis may present with symptoms of diarrhea, mucus discharge, rectal bleeding, and constipation. Complications may include pneumoperitoneum, volvulus, intestinal obstruction, intussusception, intestinal hemorrhage, and intestinal perforation. If pneumatosis cystoides intestinalis is suspected, discontinue miglitol tablets and perform the appropriate diagnostic imaging.

OVERDOSAGE

Unlike sulfonylureas or insulin, an overdose of miglitol tablets will not result in hypoglycemia. An overdose may result in transient increases in flatulence, diarrhea, and abdominal discomfort. Because of the lack of extra-intestinal effects seen with miglitol tablets, no serious systemic reactions are expected in the event of an overdose.

DOSAGE AND ADMINISTRATION

There is no fixed dosage regimen for the management of diabetes mellitus with miglitol tablets or any other pharmacologic agent. Dosage of miglitol tablets must be individualized on the basis of both effectiveness and tolerance while not exceeding the maximum recommended dosage of 100 mg 3 times daily. Miglitol tablets should be taken three times daily at the start of each main meal. Miglitol tablets should be started at 25 mg, and the dosage gradually increased both to reduce gastrointestinal adverse effects and to permit identification of the minimum dose required for adequate glycemic control of the patient.

During treatment initiation and dose titration, one-hour postprandial plasma glucose may be used to determine the therapeutic response to miglitol tablets and identify the minimum effective dose for the patient. Thereafter, glycosylated hemoglobin should be measured at intervals of approximately 3 months. The therapeutic goal should be to decrease both postprandial plasma glucose and glycosylated hemoglobin levels to normal or near normal by using the lowest effective dose of miglitol tablets, either as monotherapy or in combination with a sulfonylurea.

Initial Dosage

The recommended starting dosage of miglitol tablets is 25 mg, given orally three times daily at the start of each main meal. However, some patients may benefit by starting at 25 mg once daily to minimize gastrointestinal adverse effects, and gradually increasing the frequency of administration to 3 times daily.

Maintenance Dosage

The usual maintenance dose of miglitol tablets is 50 mg taken 3 times daily, although some patients may benefit from increasing the dose to 100 mg 3 times daily. To allow adaptation to potential gastrointestinal adverse effects, it is recommended that miglitol tablets therapy be initiated at a dosage of 25 mg 3 times daily, then gradually titrated upward to allow adaptation. After 4 to 8 weeks of the 25 mg 3 times daily regimen, the dosage should be increased to 50 mg 3 times daily for approximately three months, following which a glycosylated hemoglobin level should be measured to assess therapeutic response. If at that time, the glycosylated hemoglobin level is not satisfactory, the dosage may be further increased to 100 mg 3 times daily, the maximum recommended dosage. Pooled data from controlled studies suggest a dose-response for both HbA1c and one-hour postprandial plasma glucose throughout the recommended dosage range. However, no single study has examined the effect on glycemic control of titrating patients' doses upwards within the same study. If no further reduction in postprandial glucose or glycosylated hemoglobin levels is observed with titration to 100 mg 3 times daily, consideration should be given to lowering the dose. Once an effective and tolerated dosage is established, it should be maintained.

Maximum Dosage

The maximum recommended dosage of miglitol tablets is 100 mg 3 times daily. In one clinical trial, 200 mg 3 times daily gave additional improved glycemic control but increased the incidence of the gastrointestinal symptoms described above.

Patients Receiving Sulfonylureas

Sulfonylurea agents may cause hypoglycemia. There was no increased incidence of hypoglycemia in patients who took miglitol tablets in combination with sulfonylurea agents compared to the incidence of hypoglycemia in patients receiving sulfonylureas alone in any clinical trial. However, miglitol tablets given in combination with a sulfonylurea will cause a further lowering of blood glucose and may increase the risk of hypoglycemia due to the additive effects of the two agents. If hypoglycemia occurs, appropriate adjustments in the dosage of these agents should be made (see PRECAUTIONS).

HOW SUPPLIED

Miglitol tablets are available as 25 mg, 50 mg, and 100 mg white to off-white, circular, biconvex film-coated tablets, debossed with the logo-mark "OP" on one side and the product code on the other side, as indicated below.

 |  | Tablet Identification
Strength | NDC | Front | Back
Bottles of 30:
25 mg | 71205-935-30 | OP | 25
50 mg | 71205-936-30 | OP | 26
100 mg | 71205-937-30 | OP | 27
Bottles of 60:
25 mg | 71205-935-60 | OP | 25
50 mg | 71205-936-60 | OP | 26
100 mg | 71205-937-60 | OP | 27
Bottles of 90:
25 mg | 71205-935-90 | OP | 25
50 mg | 71205-936-90 | OP | 26
100 mg | 71205-937-90 | OP | 27
Bottles of 100:
25 mg | 71205-935-00 | OP | 25
50 mg | 71205-936-00 | OP | 26
100 mg | 71205-937-00 | OP | 27

STORAGE AND HANDLING

Store at 25°C (77°F); excursions permitted to 15° to 30°C (59° to 86°F) [see USP Controlled Room Temperature].

Manufactured by: Orient Pharma Co., Ltd. Yunlin, Taiwan

Distributed by: Westminster Pharmaceuticals, LLC

Nashville, TN 37217

Repackaged and Relabeled by: Proficient Rx LP

Thousand Oaks, CA 91320

Rev. 10/2020

PRINCIPAL DISPLAY PANEL - 25 mg Tablet Bottle Label

NDC 71205-935-30

Miglitol Tablets 25 mg

Rx only

30 Tablets

PRINCIPAL DISPLAY PANEL - 50 mg Tablet Bottle Label

NDC 71205-936-30

Miglitol Tablets 50 mg

Rx only

30 Tablets

PRINCIPAL DISPLAY PANEL - 100 mg Tablet Bottle Label

NDC 71205-937-30

Miglitol Tablets 100 mg

Rx only

30 Tablets